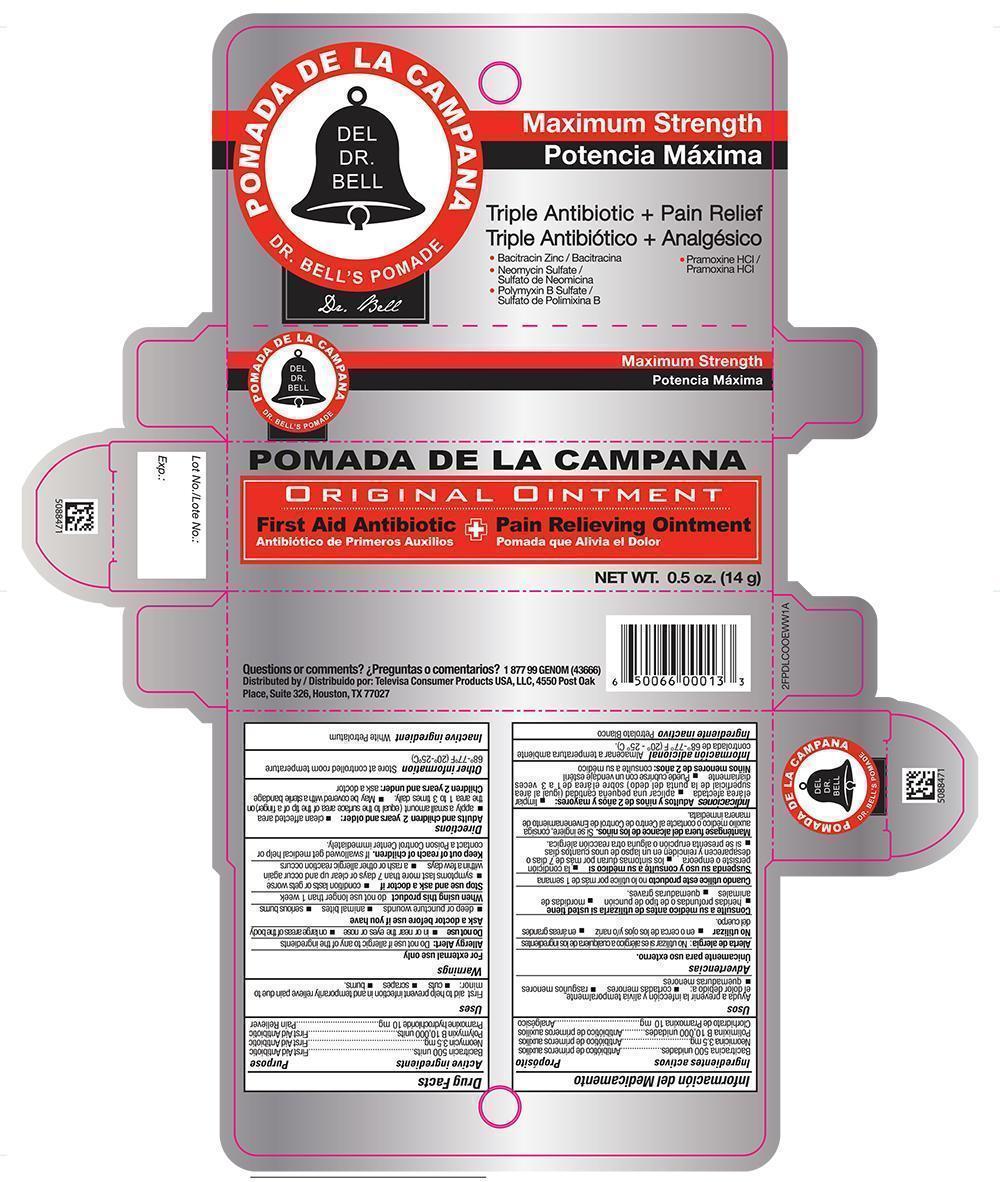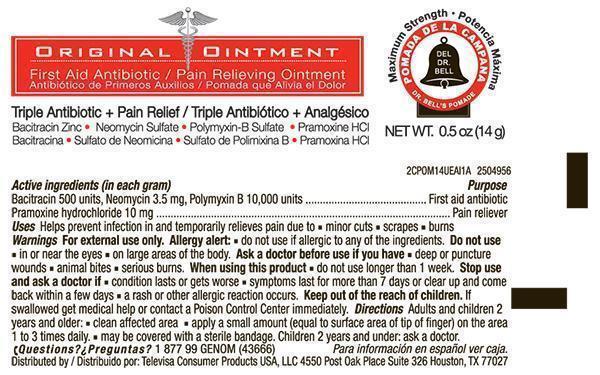 DRUG LABEL: DR BELLS POMADE
NDC: 50066-161 | Form: OINTMENT
Manufacturer: Genomma lab USA Inc.
Category: otc | Type: HUMAN OTC DRUG LABEL
Date: 20140110

ACTIVE INGREDIENTS: Bacitracin Zinc 500 [USP'U]/1 g; Polymyxin B Sulfate 10000 [USP'U]/1 g; Neomycin Sulfate 3.5 mg/1 g; PRAMOXINE HYDROCHLORIDE 10 mg/1 g
INACTIVE INGREDIENTS: Petrolatum

Drug Facts

Active ingredients (In each gram)

Bacitracin 500

Neomycin 3.5 mg

Polymyxin B 10,000 units

Pramoxine hydrochloride 10mg

Purpose

First aid antibiotic

First aid antibiotic

First aid antibiotic

Pain reliever

Uses

First aid helps prevent infection in and temporarily relieves pain due to:

- cuts
- scrapes
- burns

Warnings

For external use only

Allergy Alert: Do not use if allergic to any of the ingredients

Do not use

- in or near the eyes or nose
- on large areas of the body

Consult a doctor before use if you have

- deep or puncture wounds
- animal bites
- serious burns

When using this product

- do not use longer than 1 week

Stop use and consult a doctor if

- condition persists or gets worse
- symptoms last for more than 7 days or clear up and come back within a few days
- a rash or other allergic reaction develops

KEEP OUT OF REACH OF CHILDREN

Keep out of the reach of children. If swallowed get medical help or contact a Poison Control Center immediately.

Directions

Adults and children 2 years and older.

- clean the affected area
- apply a small amount (equal to surface area of tip of finger) on the area 1 to 3 times daily.
- may be covered with a sterile bandage

Children 2 years and under ask a doctor

Other information

- Store at a controlled room temperature 68º-77ºF (20º-25ºC)

Inactive ingredient

White Petrolatum

Principal Display Panel – Carton Label

POMADA DE LA CAMPANA

Originial Ointment

First Aid Antibiotic + Pain Relief Ointment

NET WT. 0.5 oz (14g)

Principal Display Panel – Tube Label

POMADA DE LA CAMPANA

Originial Ointment

First Aid Antibiotic + Pain Relief Ointment

Triple Antibiotic + Pain Relief

- Bacitracin Zinc
- Neomycin Sulfate
- Polymixin B Sulfate
- Pramoxine HCL

NET WT. 0.5 oz (14g)